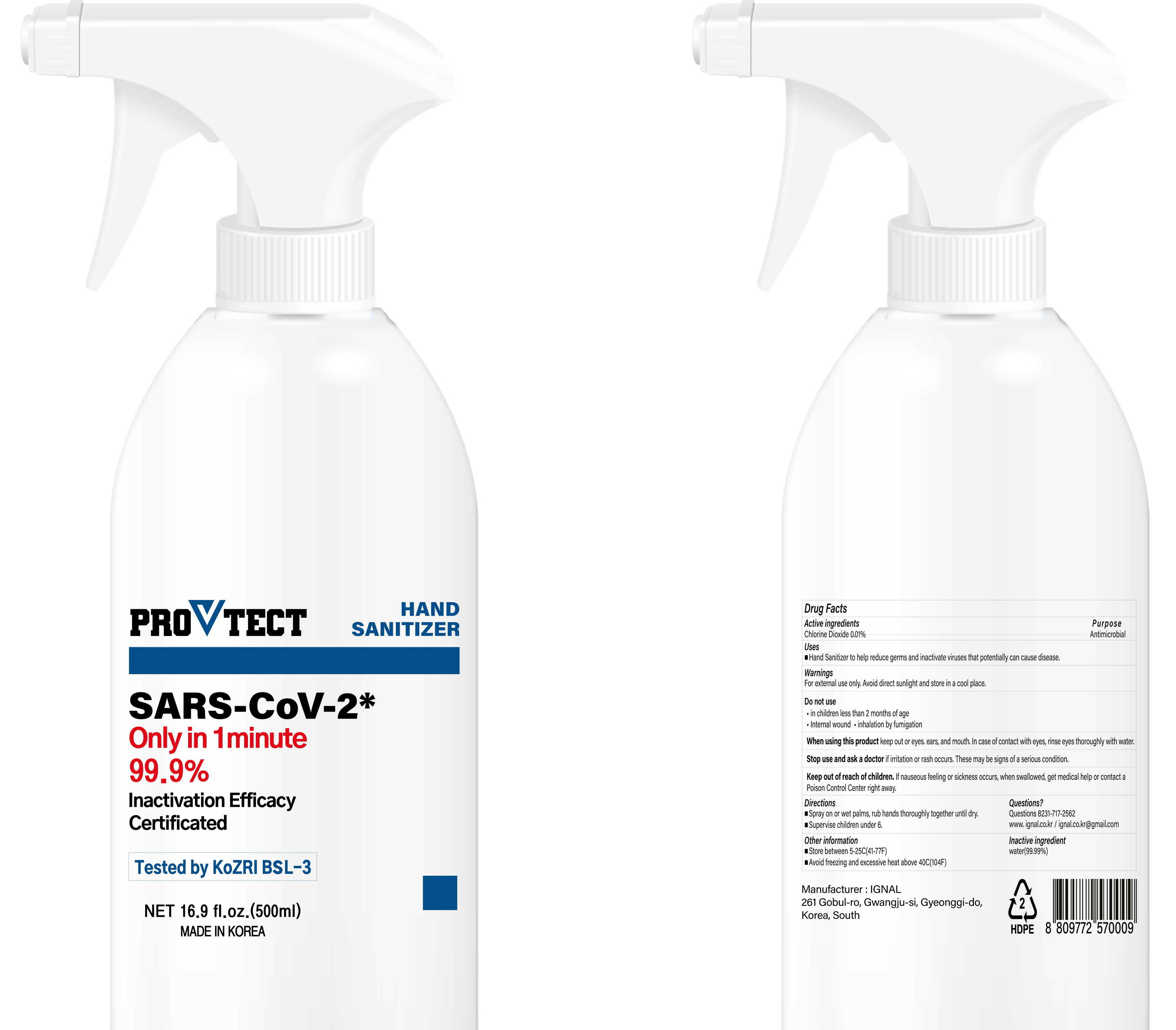 DRUG LABEL: ProVtect Hand Sanitizer
NDC: 81754-010 | Form: SPRAY
Manufacturer: Ignal
Category: otc | Type: HUMAN OTC DRUG LABEL
Date: 20210408

ACTIVE INGREDIENTS: Chlorine Dioxide 0.05 g/500 mL
INACTIVE INGREDIENTS: Water

ACTIVE INGREDIENT

Chlorine Dioxide 0.01%

INACTIVE INGREDIENT

Water

PURPOSE

Antimicrobial

WARNINGS

For external use only. Avoid direct sunlight and store in a cool place.
--------------------------------------------------------------------------------------------------------
Do not use
• in children less than 2 months of age
• internal wound • inhalation by fumigation
--------------------------------------------------------------------------------------------------------
When using this product keep out of eyes, ears, and mouth. In case of contact with eyes, rinse eyes thoroughly with water.
--------------------------------------------------------------------------------------------------------
Stop use and ask a doctor if irritation or rash occurs. These may be signs of a serious condition.
--------------------------------------------------------------------------------------------------------
Keep out of reach of children. If nauseous feeling or sickness occurs, when swallowed, get medical help or contact a Poison Control Center right away.

KEEP OUT OF REACH OF CHILDREN

If nauseous feeling or sickness occurs, when swallowed, get medical help or contact a Poison Control Center right away.

Uses

■ Hand Sanitizer help to reduce germs and inactivate viruses that potentially can cause disease.

Directions

■ Spray on or Wet palms, rub hands thoroughly together until dry.
■ Supervise children under 6.

Other information

■ Store between 5-20C (41-68F)
■ Avoid freezing and excessive heat above 40C (104F)

Questions?

Questions 8231-717-2562
www.ignal.co.kr
ignal.co.kr@gmail.com